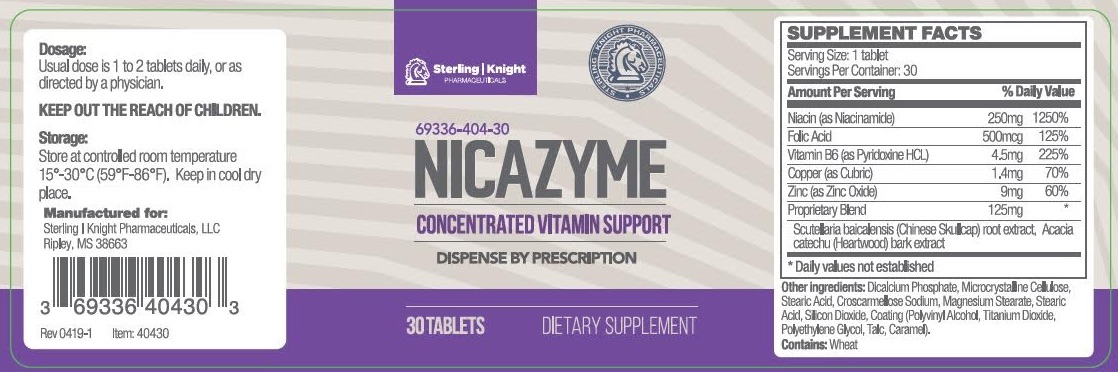 DRUG LABEL: Nicazyme
NDC: 69336-404 | Form: TABLET
Manufacturer: Sterling Knight Pharmaceuticals LLC
Category: other | Type: Dietary Supplement
Date: 20190618

ACTIVE INGREDIENTS: NIACIN 250 mg/1 1; FOLIC ACID 0.5 mg/1 1; PYRIDOXINE HYDROCHLORIDE 4.5 mg/1 1; COPPER 1.4 mg/1 1; ZINC 9 mg/1 1
INACTIVE INGREDIENTS: MICROCRYSTALLINE CELLULOSE; STEARIC ACID; MAGNESIUM STEARATE; CROSCARMELLOSE SODIUM; SILICON DIOXIDE

Nicazyme Tablets
Dietary Supplement

DESCRIPTION:

Nicazyme is an orally administered prescription dietary supplement formulation for the clinical dietary management of suboptimal nutritional status in patients where advanced supplementation is required and nutritional supplementation in physiologically stressful conditions for maintenance of good health is needed.

Nicazyme should be administered under the supervision of a licensed medical practitioner.

INDICATIONS AND USAGE:

Nicazyme is indicated for patients who are deficient in, or at risk of deficiency, in, one or more of the components of the product.

CONTRAINDICATIONS:

This product is contraindicated in patients with a known hypersensitivity to any of the ingredients.
Nicazyme should only be used under the direction and supervision of a licensed medical practitioner. Use with caution in patients that may have a medical condition, are pregnant, lactating, trying to conceive, under the age of 18, or taking medications.

WARNINGS AND PRECAUTIONS:

This product should be administered with caution in patients with a history of liver disease, jaundice or diabetes mellitus.

Folic acid above 1mg daily may obscure pernicious anemia in that hematologic remission may occur while neurological manifestations remain progressive.

Abnormal liver function test have reported in persons takings doses of 500mg or more of naicinamide.

KEEP THIS AND ALL MEDICATIONS OUT OF THE REACH OF CHILDREN.

ADVERSE REACTION:

Allergic sensitization has been reported following both oral and parental administration of folic acid.

DOSAGE AND ADMINISTRATION:

Usual dose is 1 to 2 tablets daily with or without food. Do not exceed 3 tablets per day.

STORAGE:

Store at controlled room temperature 15°-30°C (59°F-86°F). Keep in cool dry place. Call your doctor about side effects. You may report side effects to FDA at 1-800-FDA-1088. KEEP THIS OUT OF THE REACH OF CHILDREN.
HOW SUPPLIED:
Nicazyme is supplied a beige tablet dispensed in white HDPE plastic bottles of 30ct.

PACKAGE LABEL

Reserved for Professional Recommendation
All prescriptions using this product shall be pursuant to state statutes as applicable. This is not an Orange Book product. This product may be administered only under a physician’s supervision. There are no implied or explicit claims on therapeutic equivalence.

Manufactured for:
Sterling-Knight Pharmaceuticals, LLC
Ripley, MS 38663